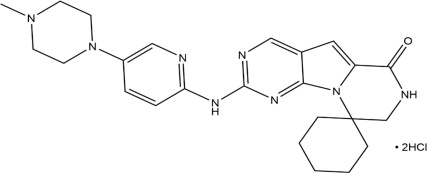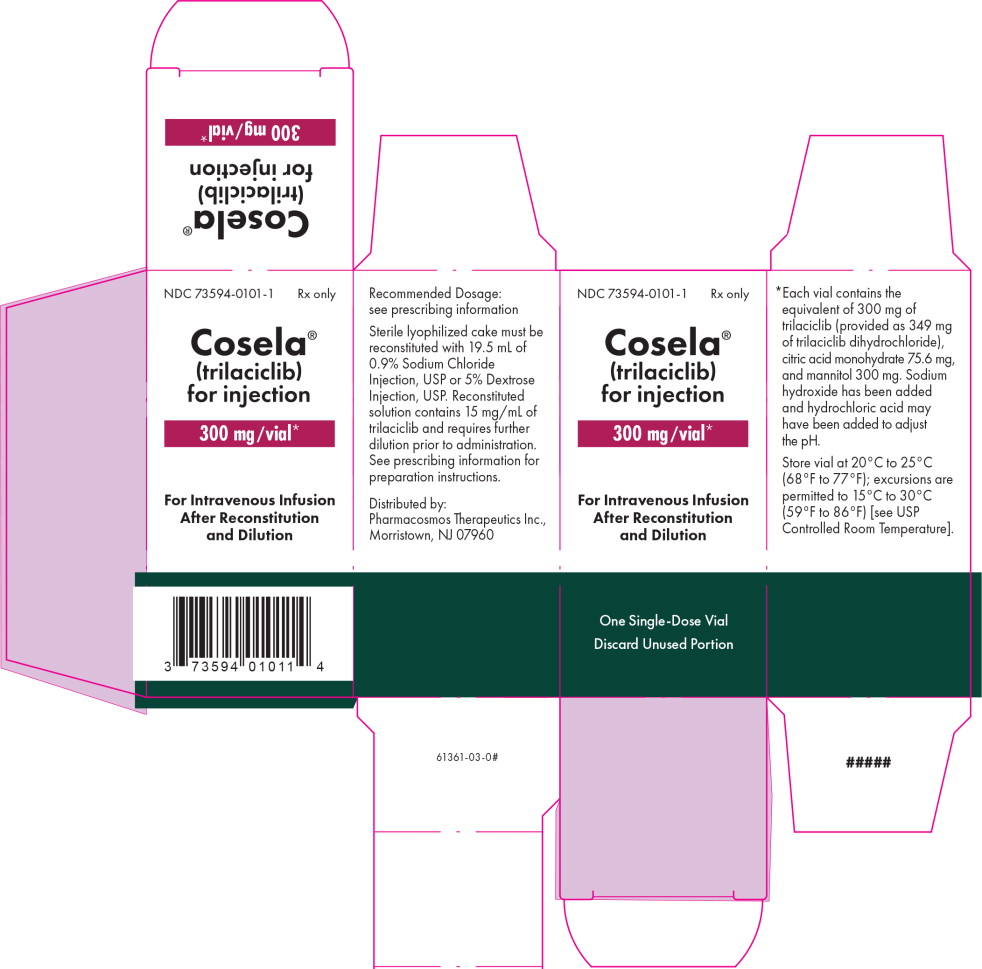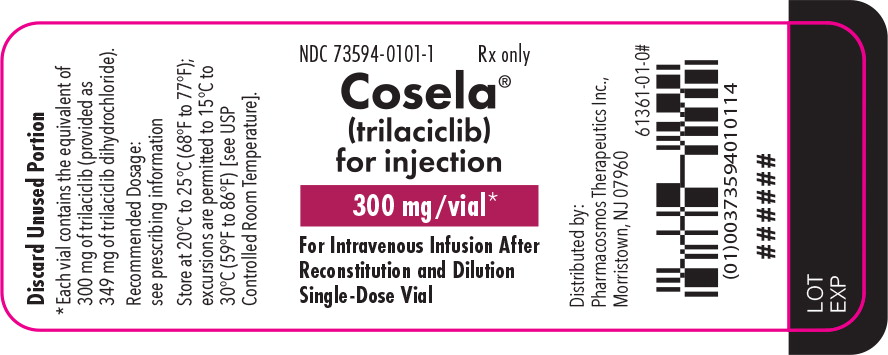 DRUG LABEL: COSELA
NDC: 73594-0101 | Form: INJECTION, POWDER, LYOPHILIZED, FOR SOLUTION
Manufacturer: Pharmacosmos Therapeutics Inc.
Category: prescription | Type: HUMAN PRESCRIPTION DRUG LABEL
Date: 20250831

ACTIVE INGREDIENTS: trilaciclib dihydrochloride 300 mg/20 mL
INACTIVE INGREDIENTS: citric acid monohydrate; mannitol; sodium hydroxide; hydrochloric acid

HIGHLIGHTS OF PRESCRIBING INFORMATION

These highlights do not include all the information needed to use COSELA safely and effectively. See full prescribing information for COSELA.
COSELA® (trilaciclib) for injection, for intravenous use
Initial U.S. Approval: 2021

1 INDICATIONS AND USAGE

COSELA is a kinase inhibitor indicated to decrease the incidence of chemotherapy-induced myelosuppression in adult patients when administered prior to a platinum/etoposide-containing regimen or topotecan-containing regimen for extensive-stage small cell lung cancer. (1)

2 DOSAGE AND ADMINISTRATION

COSELA is for intravenous use only.

The recommended dose of COSELA is 240 mg/m^2 as a 30-minute intravenous infusion completed no more than 4 hours prior to the start of chemotherapy on each day chemotherapy is administered. (2.1)

Reduce dose in patients with moderate or severe hepatic impairment. (2.2).

See Full Prescribing Information for instructions on preparation and administration. (2.3)

3 DOSAGE FORMS AND STRENGTHS

For injection: 300 mg of trilaciclib as a lyophilized cake in a single-dose vial. (3)

4 CONTRAINDICATIONS

Patients with a history of serious hypersensitivity reactions to COSELA. (4)

5 WARNINGS AND PRECAUTIONS

- Injection-Site Reactions, Including Phlebitis and Thrombophlebitis: Monitor for signs and symptoms of injection-site reactions, including phlebitis and thrombophlebitis during infusion. Stop infusion and permanently discontinue COSELA for severe or life-threatening reactions. (5.1)
- Acute Drug Hypersensitivity Reactions: Monitor for signs and symptoms of acute drug hypersensitivity reactions, including edema (facial, eye, and tongue), urticaria, pruritus, and anaphylactic reactions. Withhold COSELA for moderate reactions, and permanently discontinue for severe or life-threatening reactions. (5.2)
- Interstitial Lung Disease (ILD)/Pneumonitis: Patients treated with CDK4/6 inhibitors should be monitored for pulmonary symptoms indicative of ILD/pneumonitis. Interrupt and evaluate patients with new or worsening symptoms suspected to be due to ILD/pneumonitis. Permanently discontinue COSELA in patients with recurrent symptomatic or severe/life-threatening ILD/pneumonitis. (5.3)
- Embryo-Fetal Toxicity: Can cause fetal harm. Advise patients of the potential risk to a fetus and to use effective contraception. (5.4)

6 ADVERSE REACTIONS

The most common adverse reactions (≥10% of patients with ≥2% difference in incidence compared to placebo) were fatigue, hypocalcemia, hypokalemia, hypophosphatemia, aspartate aminotransferase increased, headache, and pneumonia. (6.1)

To report SUSPECTED ADVERSE REACTIONS, contact Pharmacosmos at 1-888-828-0655 or FDA at 1-800-FDA-1088 or www.fda.gov/medwatch.

7 DRUG INTERACTIONS

Certain OCT2, MATE1, and MATE-2K substrates: Avoid concomitant use with certain OCT2, MATE1, and MATE-2K substrates where minimal concentration changes may lead to serious or life-threatening toxicities. (7.1)

8 USE IN SPECIFIC POPULATIONS

Lactation: Advise not to breastfeed. (8.2)

FULL PRESCRIBING INFORMATION

1 INDICATIONS AND USAGE

COSELA is indicated to decrease the incidence of chemotherapy-induced myelosuppression in adult patients when administered prior to a platinum/etoposide-containing regimen or topotecan-containing regimen for extensive-stage small cell lung cancer (ES-SCLC).

2 DOSAGE AND ADMINISTRATION

2.1 Recommended Dosage

The recommended dose of COSELA is 240 mg/m^2 per dose. Administer as a 30-minute intravenous infusion completed no more than 4 hours prior to the start of chemotherapy on each day chemotherapy is administered.

The interval between doses of COSELA on sequential days should not be greater than 28 hours.

Missed Treatment Session(s)

If the COSELA dose is missed, discontinue chemotherapy on the day the COSELA dose was missed. Consider resuming both COSELA and chemotherapy on the next scheduled day for chemotherapy.

Discontinuation of Treatment

If COSELA is discontinued, wait 96 hours from the last dose of COSELA before resumption of chemotherapy only.

2.2 Dose Modification

Dose Modification for Adverse Reactions

Withhold, discontinue, or alter the administration of COSELA to manage adverse reactions as described in Table 1 [see Warnings and Precautions (5)].

Table 1: Recommended Actions for Adverse Reactions
Adverse Reaction | Severity Grade* | Recommended Action
Injection-site reactions including phlebitis and thrombophlebitis | Grade 1: Tenderness with or without symptoms (e.g., warmth, erythema, itching) | Interrupt or slow infusion of COSELA. If 0.9% Sodium Chloride Injection, USP is being used as a diluent/flush, consider changing to 5% Dextrose Injection, USP as appropriate for subsequent infusions.
Injection-site reactions including phlebitis and thrombophlebitis | Grade 2: Pain; lipodystrophy; edema; phlebitis | Interrupt infusion of COSELA. If pain not severe, follow instructions for Grade 1. Otherwise, stop infusion in extremity and rotate site of infusion to site in alternative extremity. If 0.9% Sodium Chloride Injection, USP is being used as a diluent/flush, consider changing to 5% Dextrose Injection, USP as appropriate for subsequent infusions. Central access may also be considered.
Injection-site reactions including phlebitis and thrombophlebitis | Grade 3: Ulceration or necrosis; severe tissue damage; operative intervention indicated. OR Grade 4: Life-threatening consequences; urgent interventions indicated. | Stop infusion and permanently discontinue COSELA.
Acute drug hypersensitivity reactions | Grade 2: Moderate; minimal, local, or noninvasive intervention indicated; limiting Activities of Daily Living (ADL). | Stop infusion and hold COSELA until recovery to Grade ≤1 or baseline, then consider resuming COSELA. If Grade 2 recurs, permanently discontinue COSELA.
Acute drug hypersensitivity reactions | Grade 3: Severe or medically significant but not immediately life-threatening; hospitalization or prolongation of hospitalization indicated; disabling; limiting self-care ADL. OR Grade 4: Life-threatening consequences; urgent intervention indicated. | Permanently discontinue COSELA.
Interstitial lung disease/pneumonitis | Grade 2 (symptomatic) | Hold COSELA until recovery to Grade ≤1 or baseline, then consider resuming COSELA. If Grade 2 recurs, permanently discontinue COSELA.
Interstitial lung disease/pneumonitis | Grade 3: Severe symptoms; limiting self-care ADL; oxygen indicated. OR Grade 4: Life-threatening respiratory compromise; urgent intervention indicated (e.g., tracheotomy or intubation) | Permanently discontinue COSELA.
Other toxicities | Grade 3: Severe or medically significant but not immediately life-threatening; hospitalization or prolongation of hospitalization indicated; disabling; limiting self-care ADL. | Hold COSELA until recovery to Grade ≤1 or baseline, then consider resuming COSELA. If Grade 3 recurs, permanently discontinue COSELA.
Other toxicities | Grade 4: Life-threatening consequences; urgent intervention indicated. | Permanently discontinue COSELA.
* National Cancer Institute – Common Terminology Criteria for Adverse Events (NCI-CTCAE) Version 4.03

Dose Modifications for Hepatic Impairment

Reduce the dose of COSELA to 170 mg/m^2 in patients with moderate or severe hepatic impairment (Child-Pugh classes B and C). No dose adjustment is required for patients with mild hepatic impairment (Child-Pugh class A) [see Use in Specific Populations (8.6) and Clinical Pharmacology (12.3)].

2.3 Preparation and Administration Instructions

Reconstitute and further dilute COSELA prior to intravenous infusion as outlined below. Use aseptic technique for reconstitution and dilution.

Parenteral drug products should be inspected visually for particulate matter and discoloration prior to administration, whenever solution and container permit.

Reconstitution of COSELA

- Calculate the COSELA dose based on the patient's body surface area (BSA), the total volume of reconstituted COSELA solution required, and the number of COSELA vials needed.
- Reconstitute each 300 mg vial with 19.5 mL of 0.9% Sodium Chloride Injection, USP or 5% Dextrose Injection, USP using a sterile syringe to obtain a concentration of 15 mg/mL of trilaciclib.
- Gently swirl the vial for up to 3 minutes until the sterile lyophilized cake is completely dissolved. Do not shake.
- Inspect the reconstituted solution for discoloration and particulate matter. Reconstituted COSELA solution should be a clear, yellow solution. Do not use if the reconstituted solution is discolored, cloudy, or contains visible particulates.
- Reconstituted solution in the vial can be stored at 20°C to 25°C (68°F to 77°F) for up to 4 hours prior to transfer to the infusion bag. Do not refrigerate or freeze.
- Discard any unused portion after use.

Dilution of Reconstituted COSELA Solution

- Withdraw the required volume from the vial(s) of reconstituted COSELA solution and dilute into an intravenous infusion bag containing 0.9% Sodium Chloride Injection, USP or 5% Dextrose Injection, USP. The final concentration of the diluted COSELA solution should be between 0.5 mg/mL and 3 mg/mL
- Mix diluted solution by gentle inversion. Do not shake.
- The diluted COSELA solution for infusion is a clear, yellow solution.
- If not used immediately, store the diluted COSELA solution in the intravenous infusion bag as specified in Table 2. Discard if storage time exceeds these limits. Do not refrigerate or freeze.

Table 2: Diluted COSELA Solution Storage Conditions
Intravenous Infusion Bag Material | Diluent | Diluted COSELA Storage Durationa
Polyvinyl chloride (PVC), Ethylene vinyl acetate (EVA), Polyolefin (PO), or Polyolefin/polyamide (PO/PA) | 5% Dextrose for Injection, USP | Up to 12 hours at 20°C to 25°C (68°F to 77°F)
PVC, EVA, or PO | 0.9% Sodium Chloride Injection, USP | Up to 8 hours at 20°C to 25°C (68°F to 77°F)
PO/PA | 0.9% Sodium Chloride Injection, USP | Up to 4 hours at 20°C to 25°C (68°F to 77°F)
a To ensure product stability, do not exceed specified storage durations.

Administration

- Administer diluted COSELA solution as a 30-minute intravenous infusion completed no more than 4 hours prior to the start of chemotherapy.
- Diluted COSELA solution must be administered with an infusion set, including an in-line filter (0.2 or 0.22 micron). Compatible in-line filters include polyethersulfone (PES), polyvinylidene fluoride (PVDF), and cellulose acetate (CA).
- Do not administer diluted COSELA solution with a polytetrafluorethylene (PTFE) in-line filter as it is not compatible. PTFE is acceptable for use in air vent filters.
- Do not co-administer other drugs through the same infusion line.
- Do not co-administer other drugs through a central access device unless the device supports co-administration of incompatible drugs.
- Upon completion of infusion of diluted COSELA solution, the infusion line/cannula must be flushed with at least 20 mL sterile 0.9% Sodium Chloride Injection, USP or 5% Dextrose Injection, USP.

3 DOSAGE FORMS AND STRENGTHS

For injection: Contains the equivalent of 300 mg of trilaciclib (provided as 349 mg of trilaciclib dihydrochloride) as a sterile, preservative-free, yellow, lyophilized cake in a single-dose vial for reconstitution and further dilution.

4 CONTRAINDICATIONS

COSELA is contraindicated in patients with a history of serious hypersensitivity reactions to trilaciclib. Reactions have included anaphylaxis [see Warnings and Precautions (5.2)].

5 WARNINGS AND PRECAUTIONS

5.1 Injection-Site Reactions, Including Phlebitis and Thrombophlebitis

COSELA administration can cause injection-site reactions including phlebitis and thrombophlebitis. Injection-site reactions including phlebitis and thrombophlebitis occurred in 56 (21%) of 272 patients receiving COSELA in clinical trials, including Grade 2 (10%) and Grade 3 (0.4%) adverse reactions (ARs). The median time to onset from start of COSELA was 15 days (range 1 to 542) and from the preceding dose of COSELA was 1 day (1 to 15). The median duration was 1 day (range 1 to 151 for the resolved cases). Injection-site reactions including phlebitis and thrombophlebitis resolved in 49 (88%) of the 56 patients and led to discontinuation of treatment in 3 (1%) of the 272 patients.

Monitor patients for signs and symptoms of injection-site reactions, phlebitis, and thrombophlebitis, including infusion-site pain and erythema during infusion. For mild (Grade 1) to moderate (Grade 2) injection-site reactions, flush line/cannula with at least 20 mL of sterile 0.9% Sodium Chloride Injection, USP or 5% Dextrose Injection, USP after end of infusion. For severe (Grade 3) or life-threatening (Grade 4) injection-site reactions, stop infusion and permanently discontinue COSELA [see Dosage and Administration (2.2)].

5.2 Acute Drug Hypersensitivity Reactions

COSELA administration can cause acute drug hypersensitivity reactions, including facial edema and urticaria. Acute drug hypersensitivity reactions occurred in 16 (6%) of 272 patients receiving COSELA in clinical trials, including Grade 2 reactions (2%). One patient experienced a Grade 2 anaphylactic reaction 4 days after receiving COSELA, which resolved with epinephrine, and treatment with COSELA was continued. The median time to onset from start of COSELA was 77 days (range 2 to 256) and from the preceding dose of COSELA was 1 day (range 1 to 28). The median duration was 6 days (range 1 to 69 for the resolved cases). Acute drug hypersensitivity reactions resolved in 12 (75%) of the 16 patients.

Monitor patients for signs and symptoms of acute drug hypersensitivity reactions including facial, eye, and tongue edema, urticaria, pruritus, and anaphylactic reactions. For moderate (Grade 2) acute drug hypersensitivity reactions, stop infusion and hold COSELA until the adverse reaction recovers to Grade ≤1. For severe (Grade 3) or life-threatening (Grade 4) acute drug hypersensitivity reactions, stop infusion and permanently discontinue COSELA [see Dosage and Administration (2.2)].

5.3 Interstitial Lung Disease/Pneumonitis

Severe, life-threatening, or fatal interstitial lung disease (ILD) and/or pneumonitis can occur in patients treated with cyclin-dependent kinases (CDK)4/6 inhibitors, the same drug class as COSELA. ILD/pneumonitis occurred in 1 (0.4%) of 272 patients receiving COSELA in clinical trials. The adverse reaction was Grade 3 and reported 2 months after discontinuing COSELA, in a patient receiving a confounding medication. The adverse reaction did not resolve.

Monitor patients for pulmonary symptoms indicative of ILD/pneumonitis such as cough, dyspnea, and hypoxia. For recurrent moderate (Grade 2) ILD/pneumonitis, permanently discontinue COSELA. For severe (Grade 3) or life-threatening (Grade 4) ILD/pneumonitis, permanently discontinue COSELA [see Dosage and Administration (2.2)].

5.4 Embryo-Fetal Toxicity

Based on its mechanism of action, COSELA can cause fetal harm when administered to a pregnant woman. Females of reproductive potential should use an effective method of contraception during treatment with COSELA and for at least 3 weeks after the final dose [see Use in Specific Populations (8.1, 8.3)].

6 ADVERSE REACTIONS

The following clinically significant adverse reactions are described elsewhere in the label:

- Injection-Site Reactions, including phlebitis and thrombophlebitis [see Warnings and Precautions (5.1)]
- Acute Drug Hypersensitivity Reactions [see Warnings and Precautions (5.2)]
- ILD/Pneumonitis [see Warnings and Precautions (5.3)]

6.1 Clinical Trials Experience

Because clinical trials are conducted under widely varying conditions, adverse reaction rates observed in the clinical trials of a drug cannot be directly compared with rates in the clinical trials of another drug and may not reflect the rates observed in clinical practice.

The safety of COSELA was evaluated in Studies 1, 2, and 3 [see Clinical Studies (14)]. Patients received COSELA 240 mg/m^2 by 30-minute intravenous infusion prior to chemotherapy on each chemotherapy day. The data described in this section reflect exposure to COSELA among 240 patients (122 patients in the trilaciclib group and 118 patients in the placebo group) being treated for extensive stage-small cell lung cancer (ES-SCLC) in 3 randomized, double-blind, placebo-controlled trials: 32 patients with treatment naïve ES-SCLC received carboplatin (AUC 5 Day 1) + etoposide (100 mg/m^2 Days 1-3) every 21 days; 58 received carboplatin (AUC 5 Day 1) + etoposide (100 mg/m^2 Days 1-3) every 21 days + atezolizumab (1200 mg on Day 1) every 21 days; 32 patients with previously treated ES-SCLC received topotecan (1.5 mg/m^2 Days 1-5) every 21 days.

Study 1: COSELA Prior to Etoposide, Carboplatin, and Atezolizumab (E/P/A)

Patients with newly diagnosed ES-SCLC not previously treated with chemotherapy

Study 1 (G1T28-05; NCT03041311) was an international, randomized (1:1), double-blind, placebo-controlled study of COSELA or placebo administered prior to treatment with etoposide, carboplatin, and atezolizumab (E/P/A) for patients with newly diagnosed ES-SCLC not previously treated with chemotherapy. The data presented below are for the 105 patients who received study treatment.

Eighty-five percent of patients receiving COSELA and 91% receiving placebo completed 4 cycles of induction therapy.

Study 2: COSELA Prior to Etoposide and Carboplatin (E/P)

Patients with newly diagnosed ES-SCLC not previously treated with chemotherapy

Study 2 (G1T28-02; NCT02499770) was an international, randomized (1:1), double-blind, placebo-controlled study of COSELA or placebo administered prior to treatment with etoposide and carboplatin (E/P) for patients with newly diagnosed ES-SCLC not previously treated with chemotherapy. The data presented below are for the 75 patients who received study treatment.

Seventy-six percent of patients in the COSELA group and 87% of patients in the placebo group completed at least 4 cycles of therapy. The median duration of treatment was 6 cycles in each treatment group.

Study 3: COSELA Prior to Topotecan

Patients with ES-SCLC previously treated with chemotherapy

Study 3 (G1T28-03; NCT02514447) was an international, randomized (2:1), double-blind, placebo-controlled study of COSELA or placebo administered prior to treatment with topotecan for patients with ES-SCLC previously treated with chemotherapy. The data presented below are for the 60 patients who received study treatment with the 1.5 mg/m^2 dose of topotecan.

Thirty-eight percent of patients receiving COSELA and 29% of patients receiving placebo completed 5 or more cycles of therapy. The median duration of treatment was 3 cycles in each treatment group.

Integrated Safety Analysis

The adverse reaction summary presented in Table 3 are pooled safety results from Studies 1, 2, and 3. The patients included in the pooling are those randomized patients that received at least 1 dose of COSELA (122 patients) or placebo (118 patients).

Seventy-one percent of patients receiving COSELA and 78% of patients receiving placebo completed at least 4 cycles of therapy. The median duration of treatment was the same (4 cycles) for patients receiving COSELA and placebo.

Serious adverse reactions occurred in 30% of patients receiving COSELA. Serious adverse reactions reported in >3% of patients who received COSELA included respiratory failure, hemorrhage, and thrombosis.

Permanent discontinuation due to an adverse reaction occurred in 9% of patients who received COSELA. Adverse reactions leading to permanent discontinuation of any study treatment for patients receiving COSELA included pneumonia (2%), asthenia (2%), injection-site reaction, thrombocytopenia, cerebrovascular accident, ischemic stroke, infusion-related reaction, respiratory failure, and myositis (<1% each).

Fatal adverse reactions were observed in 5% of patients receiving COSELA. Fatal adverse reactions for patients receiving COSELA included pneumonia (2%), respiratory failure (2%), acute respiratory failure (<1%), hemoptysis (<1%), and cerebrovascular accident (<1%).

Infusion interruptions due to an adverse reaction occurred in 4.1% of patients who received COSELA.

The most common adverse reactions (≥10%) were fatigue, hypocalcemia, hypokalemia, hypophosphatemia, aspartate aminotransferase increased, headache, and pneumonia. The most frequently reported Grade ≥3 adverse reaction (≥5%) in patients receiving COSELA occurring at the same or higher incidence than in patients receiving placebo was hypophosphatemia.

The most common adverse reactions reported in at least 5% of patients receiving COSELA with a ≥2% higher incidence compared to patients receiving placebo are shown in Table 3.

Table 3: Adverse Reactions in ≥5% Patients with SCLC Receiving COSELA (with ≥2% Higher Incidence in COSELA Compared to Placebo)
Adverse Reaction | COSELA (N=122) |  | Placebo (N=118)
Adverse Reaction | All Gradesa (%) | Grade ≥3 (%) | All Gradesa (%) | Grade ≥3 (%)
Fatigue | 34 | 3 | 27 | 2
Hypocalcemiab | 24 | <1 | 21 | <1
Hypokalemiac | 22 | 6 | 18 | 3
Hypophosphatemiad | 21 | 7 | 16 | 2
Aspartate aminotransferase increasede | 17 | <1 | 14 | <1
Headache | 13 | 0 | 9 | 0
Pneumonia | 10 | 7 | 8 | 7
Rash | 9 | <1 | 6 | 0
Infusion-related reaction | 8 | 0 | 2 | 0
Edema peripheral | 7 | 0 | 4 | <1
Abdominal pain upper | 7 | 0 | 3 | 0
Thrombosis | 7 | 3 | 2 | 2
Hyperglycemia | 6 | 2 | 3 | 0
a Graded per NCI CTCAE v4.03
b Hypocalcemia=calcium decreased (lab) or treatment-emergent adverse event (TEAE) preferred term 'Hypocalcemia'
c Hypokalemia=potassium decreased (lab) or TEAE preferred terms 'Hypokalemia,' 'Blood potassium decreased'
d Hypophosphatemia=phosphate decreased (lab) or TEAE preferred terms 'Hypophosphatemia,' 'Blood phosphorus decreased'
e Aspartate aminotransferase increased=aspartate aminotransferase increased (lab) or TEAE preferred term 'Blood aspartate aminotransferase increased'

Grade 3/4 hematological adverse reactions occurring in patients treated with COSELA and placebo included neutropenia (32% and 69%), febrile neutropenia (3% and 9%), anemia (16% and 34%), thrombocytopenia (18% and 33%), leukopenia (4% and 17%), and lymphopenia (<1% and <1%), respectively.

7 DRUG INTERACTIONS

7.1 Effect of COSELA on Other Drugs, Certain OCT2, MATE1, and MATE-2K Substrates

COSELA is an inhibitor of OCT2, MATE1, and MATE-2K. Co-administration of COSELA may increase the concentration or net accumulation of OCT2, MATE1, and MATE-2K substrates in the kidney (e.g., dofetilide, dalfampridine, and cisplatin) [see Clinical Pharmacology (12.3)].

Refer to the prescribing information for these concomitant medications for assessing the benefit and risk of concomitant use of COSELA.

Table 4: Potentially Significant Drug Interactions with COSELA
Drugs | Recommendations | Comments
Dofetilide | The potential benefits of taking COSELA concurrently with dofetilide should be considered against the risk of QT interval prolongation. | Increased dofetilide blood levels may occur in patients who are also receiving COSELA. Increased plasma concentrations of dofetilide may cause serious ventricular arrhythmias associated with QT interval prolongation, including torsade de pointes.
Dalfampridine | The potential benefits of taking COSELA concurrently with dalfampridine should be considered against the risk of seizures in these patients. | Increased dalfampridine blood levels may occur in patients who are also receiving COSELA. Elevated levels of dalfampridine increase the risk of seizure.
Cisplatin | Closely monitor for nephrotoxicity. | Concurrent treatment with COSELA may increase the exposure and alter the net accumulation of cisplatin in the kidney, which may associate with dose-related nephrotoxicity.

8 USE IN SPECIFIC POPULATIONS

8.1 Pregnancy

Risk Summary

Based on the mechanism of action, COSELA can cause fetal harm when administered to a pregnant woman [see Clinical Pharmacology (12)]. There are no available human or animal data on COSELA use to evaluate for a drug-associated risk of major birth defects, miscarriage, or adverse maternal or fetal outcomes. Advise pregnant women of the potential risk to a fetus.

The background risk of major birth defects and miscarriage for the indicated population is unknown. All pregnancies have a background risk of birth defect, loss, or other adverse outcomes. However, the background risk of major birth defects is 2% to 4% and of miscarriage is 15% to 20% of clinically recognized pregnancies in the United States general population.

8.2 Lactation

Risk Summary

There are no data on the presence of trilaciclib in either human or animal milk, the effects on the breastfed child or the effects on milk production. Because of the potential for serious adverse reactions in breastfed children, advise lactating women to not breastfeed while taking COSELA and for at least 3 weeks after the last dose.

8.3 Females and Males of Reproductive Potential

Pregnancy Testing

Based on its mechanism of action, COSELA can cause fetal harm if administered to a pregnant woman [see Use in Specific Populations (8.1)]. Pregnancy testing is recommended for females of reproductive potential prior to initiating COSELA.

Contraception

COSELA can cause fetal harm when administered to pregnant women [see Use in Specific Populations (8.1)]. Advise female patients of reproductive potential to use effective contraception during treatment with COSELA and for at least 3 weeks after the final dose.

Infertility

No studies have been performed in humans to evaluate the effects of COSELA on fertility in either sex.

Based on animal toxicology studies, COSELA may impair fertility in females of reproductive potential [see Nonclinical Toxicology (13)].

8.4 Pediatric Use

Safety and effectiveness in pediatric patients have not been established.

8.5 Geriatric Use

In the pooled efficacy dataset from Studies 1, 2, and 3, 46% of 123 patients randomized to COSELA were ≥65 years of age, and 49% of 119 patients randomized to placebo were ≥65 years of age. No overall differences in safety or effectiveness of COSELA were observed between these patients and younger patients.

8.6 Hepatic Impairment

Reduce the dose of COSELA to 170 mg/m^2 in patients with moderate or severe hepatic impairment (Child-Pugh classes B and C). No dose adjustment is required in patients with mild hepatic impairment (Child-Pugh class A) [see Dosage and Administration (2.2)].

Trilaciclib is mainly metabolized in the liver. Trilaciclib exposure increased with moderate and severe hepatic impairment (Child-Pugh classes B and C) [see Clinical Pharmacology (12.3)].

11 DESCRIPTION

COSELA for injection contains trilaciclib dihydrochloride, a kinase inhibitor.

The chemical name for trilaciclib is 2'-{[5-(4-methylpiperazin-1-yl)pyridin-2-yl]amino}-7',8'-dihydro-6'H-spiro[cyclohexane-1,9'-pyrazino[1',2':1,5]pyrrolo[2,3-d]pyrimidin]-6'-one.

Trilaciclib dihydrochloride is a water-soluble yellow solid, with molecular formula of C24H30N8O•2HCl, a molecular weight of 519.48 g/mol (Free base: 446.56 g/mol), and the following chemical structure:

COSELA (trilaciclib) for injection is a sterile, preservative-free, yellow lyophilized cake in a single-dose vial for intravenous infusion after reconstitution and dilution.

Each single-dose vial contains the equivalent of 300 mg of trilaciclib (provided as 349 mg of trilaciclib dihydrochloride) and the following inactive ingredients: citric acid monohydrate (75.6 mg) and mannitol (300 mg); hydrochloric acid and sodium hydroxide to adjust pH.

12 CLINICAL PHARMACOLOGY

12.1 Mechanism of Action

Trilaciclib is a transient inhibitor of CDK 4 and 6. Hematopoietic stem and progenitor cells (HSPCs) in the bone marrow give rise to circulating neutrophils, RBCs, and platelets. HSPC proliferation is dependent on CDK4/6 activity.

12.2 Pharmacodynamics

Bone Marrow

Trilaciclib exhibited dose-dependent inhibition of CD45+/CD3+ lymphocyte proliferation following administration of single-dose COSELA 96 or 192 mg/m^2 (0.4 or 0.8 times the approved recommended dose) in healthy subjects.

Trilaciclib increased the percentage of cells arrested in G1 up to 32 hours post-infusion for all bone marrow progenitor subsets evaluated (hematopoietic stem cell/multipotent progenitor, oligopotent progenitor, monocyte lineage, granulocyte lineage, erythroid lineage, and megakaryocyte lineage) following a single dose of COSELA 192 mg/m^2 (0.8 times the approved recommended dose) in healthy subjects. Partial recovery of the total bone marrow with resumption of proliferation of the bone marrow progenitor subsets was observed by 32 hours post-dose. This transient G1 arrest of hematopoietic stem cells contributed to the myeloprotective effect of trilaciclib.

Cardiac Electrophysiology

COSELA is associated with dose-dependent and delayed increase in the QTc interval. The underlying mechanism of the delayed QT effect is unknown. At the clinical dose of 240 mg/m^2, COSELA did not have a clinically relevant effect on QTc (i.e., >10 msec). QTc prolongation was observed at higher doses.

12.3 Pharmacokinetics

The maximum concentration (Cmax) increased proportionally whereas the total plasma exposure (AUC0-last) increased slightly greater than proportional over a dosage range of trilaciclib 200 mg/m^2 to 700 mg/m^2 (0.83 to 2.9 times the approved recommended dose). There was no accumulation of trilaciclib following repeated dosing.

Distribution

The in vitro human plasma protein binding of trilaciclib is 69% and appeared independent of trilaciclib concentration from 0.75 to 3.0 μg/mL. The blood/plasma ratio ranged from 1.21 to 1.53 for trilaciclib across concentrations of 0.5 μg/mL to 50 μg/mL in vitro. The volume of distribution at steady state was 1130 L.

Elimination

The mean terminal half-life of trilaciclib is approximately 14 hours. Clearance was estimated to be 158 L/hr.

Metabolism

Trilaciclib undergoes extensive metabolism. Trilaciclib is the predominant circulating compound in plasma following intravenous administration, representing ~50% of plasma total radioactivity. In vitro studies indicated that trilaciclib is primarily metabolized by aldehyde oxidase (AO), cytochrome P450 (CYP) 3A4 and CYP2C8.

Excretion

After a single dose of radiolabeled trilaciclib 192 mg/m^2 (0.8 times the approved recommended dosage), approximately 79.1% of the dose was recovered in feces (7% unchanged) and 14% was recovered in urine (2% unchanged).

Trilaciclib is eliminated mainly via the fecal route, with a small contribution of the renal route.

Specific Populations

No clinically significant differences in the pharmacokinetics of trilaciclib were observed based on age (range: 19 to 80 years), sex, race, mild to moderate renal impairment (30 to 89 mL/min/1.73 m^2 measured by estimated glomerular filtration rate [eGFR]), or mild hepatic impairment (total bilirubin ≤ULN and AST >ULN, or total bilirubin >1.0 to 1.5 × ULN, irrespective of AST). The effect of severe renal impairment (<30 mL/min/1.73 m^2), end stage renal disease, or dialysis on trilaciclib pharmacokinetics has not been studied.

Subjects with Hepatic Impairment

Trilaciclib unbound AUCinf increased by 40% and 63%, respectively, in subjects with moderate and severe hepatic impairment (Child-Pugh classes B and C). No clinically significant differences were observed in trilaciclib systemic exposures in subjects with mild hepatic impairment [see Dosage and Administration (2.2) and Use in Specific Populations (8.6)].

Drug Interaction Studies

Clinical Studies

Cytochrome P450 (CYP) Enzymes: There were no clinically significant differences in trilaciclib pharmacokinetics when used concomitantly with itraconazole (strong CYP3A inhibitor) or rifampin (strong CYP3A inducer). There were no clinically significant differences in midazolam (CYP3A substrate) pharmacokinetics when used concomitantly with trilaciclib.

Transporter Systems: Concomitant use of trilaciclib increased metformin (OCT2, MATE1, and MATE-2K substrate) AUCinf and Cmax by approximately 65% and 81%, respectively. Renal clearance of metformin was decreased by 37%. There were no clinically significant differences in topotecan (MATE1 and MATE-2K substrate) pharmacokinetics when used concomitantly with trilaciclib.

In Vitro Studies

CYP Enzymes: Trilaciclib did not inhibit CYP1A2, CYP2B6, CYP2C8, CYP2C9, CYP2C19, or CYP2D6. Trilaciclib is an inducer for CYP1A2, and is not an inducer for CYP2B6 or CYP3A4.

Transporter Systems: Trilaciclib did not inhibit P-glycoprotein (P-gp), breast cancer resistance protein (BCRP), organic anion transporting polypeptide 1B1 (OATP1B1), OATP1B3, OAT1, or OAT3. Trilaciclib was a substrate of BCRP and P-gp, but not bile salt export pump (BSEP), MATE1, MATE-2K, or OCT.

13 NONCLINICAL TOXICOLOGY

13.1 Carcinogenesis, Mutagenesis, Impairment of Fertility

Carcinogenesis studies have not been conducted with trilaciclib.

Trilaciclib was negative for mutagenic potential in a bacterial reverse mutation (Ames) assay and negative for clastogenic potential in an in vitro histone H2AX phosphorylation assay in primary human fibroblasts. Trilaciclib increased the frequency of micronucleus formation in human lymphocytes in vitro. Clastogenic potential of trilaciclib was not assessed in vivo.

Fertility studies have not been performed to evaluate the effects of trilaciclib. Treatment with trilaciclib in female rats and dogs resulted in reductions in mean ovary and uterus weights at clinically relevant exposures, which were reversible after a two-week drug-free recovery period.

14 CLINICAL STUDIES

The efficacy of COSELA was established in three randomized, double-blind, placebo-controlled trials in patients with extensive stage-small cell lung cancer (ES-SCLC). Study 1 (G1T28-05; NCT03041311) enrolled adult patients receiving carboplatin, etoposide, and atezolizumab for newly diagnosed ES-SCLC. Study 2 (G1T28-02; NCT02499770) enrolled adult patients receiving etoposide/carboplatin for newly diagnosed ES-SCLC. Study 3 (G1T28-03; NCT02514447) enrolled adult patients receiving topotecan for previously treated ES-SCLC.

During Cycle 1, all three studies prohibited primary prophylactic granulocyte-colony stimulating factor (G-CSF) and erythropoiesis-stimulating agent (ESA) use. Both ESAs and prophylactic G-CSF were allowed from Cycle 2 onwards as clinically indicated. Therapeutic G-CSF, RBC, and platelet transfusions were allowed at any time during the studies as clinically indicated.

Study 1: COSELA Prior to Etoposide, Carboplatin, and Atezolizumab (E/P/A)

Patients with newly diagnosed ES-SCLC not previously treated with chemotherapy

Study 1 (G1T28-05) was a randomized (1:1), double-blind, placebo-controlled study of COSELA or placebo administered prior to treatment with etoposide, carboplatin, and atezolizumab (E/P/A) for patients with newly diagnosed ES-SCLC not previously treated with chemotherapy.

A total of 107 patients were randomized to receive COSELA (n=54) or placebo (n=53) prior to administration of E/P/A; patients were stratified by Eastern Cooperative Oncology Group (ECOG) performance status (0 to 1 vs 2) and the presence of brain metastases. Carboplatin (AUC 5) and atezolizumab (1200 mg) were administered on Day 1 and etoposide (100 mg/m^2) and COSELA (240 mg/m^2) or placebo were administered on Days 1, 2, and 3 of a 21-day cycle for a maximum of 4 cycles (induction). After induction, maintenance atezolizumab (1200 mg) monotherapy on Day 1 of a 21-day cycle continued until disease progression or unacceptable toxicity. COSELA was not administered during maintenance.

The study population characteristics were: median age 64 years (range: 45 to 83); 70% male; 97% white; 14% ECOG performance status 2; 28% with a history of brain metastases; 38% current smokers; 46% lactate dehydrogenase (LDH) >ULN.

The mean relative dose intensities (RDIs) for E/P/A in patients receiving COSELA were 93%, 95%, and 93%, respectively. The mean RDIs for E/P/A in patients receiving placebo were 88%, 89%, and 91%, respectively. Dose reductions of carboplatin occurred in 2% of patients receiving COSELA and in 25% of patients receiving placebo; dose reductions of etoposide occurred in 6% of patients receiving COSELA and in 26% of patients receiving placebo. No dose reduction was allowed for COSELA or atezolizumab.

The study demonstrated a statistically significantly shorter duration of severe neutropenia (DSN) in Cycle 1 (0 vs 4 days) and a lower proportion of patients with severe neutropenia (SN) (2% vs 49%) in patients receiving COSELA compared with placebo (Table 5). Nineteen percent of patients receiving COSELA had Grade 3 or 4 decreased hemoglobin compared with 28% of patients receiving placebo (adjusted relative risk 0.663 [95% CI: 0.336, 1.310]). The rate of RBC transfusions over time was 1.7/100 weeks for patients receiving COSELA and 2.6/100 weeks for patients receiving placebo (adjusted relative risk was not estimable). Six percent of patients receiving COSELA received erythropoiesis-stimulating agents (ESAs) compared with 11% of patients receiving placebo (adjusted relative risk 0.529 [95% CI: 0.145, 1.927]).

Table 5: Study 1: Myeloprotective Efficacy Results in Patients Treated with COSELA or Placebo Prior to Chemotherapy (Intent-to-Treat Analysis)
Endpoint | COSELA 240 mg/m^2 (N=54) | Placebo (N=53) | Treatment Effecta (Mean Difference* or Adjusted Relative Risk) (95% CI) | Adjusted 1-sided p-valueb
Primary Endpoints
DSN in Cycle 1 (days): mean (SD) | 0 (1.0) | 4 (4.7) | -3.6* (-4.9, -2.3) | <0.0001
Number (%) of patients with severe neutropenia | 1 (1.9%) | 26 (49.1%) | 0.038 (0.008, 0.195) | <0.0001
Key Secondary Endpoints
Number of all-cause dose reductions, event rate per cycle | 0.021 | 0.085 | 0.242 (0.079, 0.742) | 0.0195
Number (%) of patients with RBC transfusion on/after 5 weeks | 7 (13.0%) | 11 (20.8%) | 0.642 (0.294, 1.404) | --
Number (%) of patients with G-CSF administration | 16 (29.6%) | 25 (47.2%) | 0.646 (0.403, 1.034) | --
ANCOVA=analysis of covariance; CI=confidence interval; DSN=duration of severe neutropenia; G-CSF=granulocyte colony-stimulating factor; N=total number of patients in each treatment group; RBC=red blood cell; SD=standard deviation
a The following statistical models were used to assess treatment effects: non-parametric ANCOVA (DSN in Cycle 1); modified Poisson regression (occurrence of SN and RBC transfusion on/after 5 weeks); negative binomial regression (number of all-cause dose reductions). All models included the following as covariates: ECOG status, presence of brain metastases, and the corresponding baseline laboratory values.
b One-sided adjusted p-value obtained from a Hochberg-based gatekeeping procedure.

Study 2: COSELA Prior to Etoposide and Carboplatin

Patients with newly diagnosed ES-SCLC not previously treated with chemotherapy

Study 2 (G1T28-02) was a randomized (1:1), double-blind, placebo-controlled evaluation of COSELA or placebo administered prior to treatment with etoposide and carboplatin (E/P) for patients with newly diagnosed ES-SCLC not previously treated with chemotherapy. A total of 77 patients were randomized to COSELA (n=39) or placebo (n=38) and stratified by ECOG performance status (0 to 1 vs 2). Carboplatin (AUC 5) was administered on Day 1 and etoposide (100 mg/m^2) and COSELA (240 mg/m^2) or placebo were administered on Days 1, 2, and 3 of a 21-day cycle until disease progression or unacceptable toxicity.

Ten percent of patients receiving COSELA had Grade 3 or 4 decreased hemoglobin compared with 18% of patients receiving placebo. The rate of RBC transfusions over time was 0.5/100 weeks for patients receiving COSELA and 1.9/100 weeks for patients receiving placebo. Three percent of patients receiving COSELA received ESAs compared with 5% of patients receiving placebo.

Table 6: Study 2: Myeloprotective Efficacy Results in Patients Treated with COSELA or Placebo Prior to Chemotherapy (Intent-to-Treat Analysis)
Endpoint | COSELA 240 mg/m^2 (N=39) | Placebo (N=38)
DSN in Cycle 1 (days): mean (SD) | 0 (0.5) | 3 (3.9)
Number (%) of patients with severe neutropenia | 2 (5.1%) | 16 (42.1%)
Number of all-cause dose reductions, event rate per cycle | 0.022 | 0.084
Number (%) of patients with RBC transfusion on/after 5 weeks | 2 (5.1%) | 9 (23.7%)
Number (%) of patients with G-CSF administration | 4 (10.3%) | 24 (63.2%)
DSN=duration of severe neutropenia; G-CSF=granulocyte colony-stimulating factor; N=total number of patients in each treatment group; RBC=red blood cell; SD=standard deviation

Study 3: COSELA Prior to Topotecan

Patients with ES-SCLC previously treated with chemotherapy

Study 3 (G1T28-03) included a randomized, double-blind, placebo-controlled evaluation of COSELA or placebo administered prior to topotecan in patients with ES-SCLC previously treated with chemotherapy. A total of 61 patients were randomized to COSELA (n=32) or placebo (n=29). Patients were stratified by ECOG performance status (0 to 1 vs 2) and sensitivity to first-line treatment. Topotecan (1.5 mg/m^2) and COSELA (240 mg/m^2) or placebo were administered on Days 1-5 of a 21-day cycle. Treatment was administered until disease progression or unacceptable toxicity.

Thirty-eight percent of patients receiving COSELA had Grade 3 or 4 decreased hemoglobin compared with 59% of patients receiving placebo. The rate of RBC transfusions over time was 2.6/100 weeks for patients receiving COSELA and 6.3/100 weeks for patients receiving placebo. Three percent of patients receiving COSELA received ESAs compared with 21% of patients receiving placebo.

Table 7: Study 3: Myeloprotective Efficacy Results in Patients Treated with COSELA or Placebo Prior to Chemotherapy (Intent-to-Treat Analysis)
Endpoint | COSELA 240 mg/m^2 (N=32) | Placebo (N=29)
Primary Endpoints
DSN in Cycle 1 (days): mean (SD) | 2 (3.9) | 7 (6.2)
Number (%) of patients with severe neutropenia | 13 (40.6%) | 22 (75.9%)
Key Secondary Endpoints
Number of all-cause dose reductions, event rate per cycle | 0.051 | 0.116
Number (%) of patients with RBC transfusion on/after 5 weeks | 10 (31.3%) | 12 (41.4%)
Number (%) of patients with G-CSF administration | 16 (50.0%) | 19 (65.5%)
Number (%) of patients with platelet transfusion | 8 (25.0%) | 9 (31.0%)
DSN=duration of severe neutropenia; G-CSF=granulocyte colony-stimulating factor; N=total number of patients in each treatment group; RBC=red blood cell; SD=standard deviation

Patient Subgroups

Treatment efficacy was examined across different subgroups, including those quantifying the risk of febrile neutropenia, anemia, and RBC transfusions; results were consistent across subgroups.

16 HOW SUPPLIED/STORAGE AND HANDLING

16.1 How Supplied

COSELA (trilaciclib) for injection is a yellow lyophilized cake supplied in a single-dose vial. Each carton (NDC 73594-0101-1) contains one 300 mg strength single-dose vial.

16.2 Storage and Handling

Store COSELA vials at 20°C to 25°C (68°F to 77°F); excursions are permitted to 15°C to 30°C (59°F to 86°F) [see USP Controlled Room Temperature].

The vial stopper is not made with natural rubber latex.

17 PATIENT COUNSELING INFORMATION

Injection-Site Reactions, Including Phlebitis and Thrombophlebitis

Inform patients of the signs and symptoms of injection-site reactions, including phlebitis and thrombophlebitis. Advise patients to contact their healthcare provider immediately for signs and symptoms of injection-site reactions, including phlebitis and thrombophlebitis [see Warnings and Precautions (5.1)].

Acute Drug Hypersensitivity Reactions

Advise patients to contact their healthcare provider immediately for signs and symptoms of acute drug hypersensitivity reactions including facial, eye, and tongue edema, urticaria, pruritis, and anaphylactic reactions [see Warnings and Precautions (5.2)].

Interstitial Lung Disease/Pneumonitis

Advise patients to immediately report new or worsening respiratory symptoms [see Warnings and Precautions (5.3) and Dosage and Administration (2.2)].

Embryo-Fetal Toxicity

Advise females of reproductive potential of the potential risk to a fetus and to inform their healthcare provider of a known or suspected pregnancy [see Use in Specific Populations (8.1)].

Advise females of reproductive potential to use effective contraception during treatment with COSELA and for at least 3 weeks after the final dose [see Use in Specific Populations (8.1, 8.3)].

Lactation

Advise women not to breastfeed during treatment with COSELA and for at least 3 weeks after the final dose of COSELA [see Use in Specific Populations (8.2)].

Drug Interactions

Advise patients to inform their healthcare providers of all concomitant medications, including prescription medicines, over-the-counter drugs, vitamins, and herbal products [see Drug Interactions (7)].

Distributed by:
Pharmacosmos Therapeutics Inc.,
Morristown, NJ 07960

COSELA® is a registered trademark of Pharmacosmos Holding A/S
©2025 Pharmacosmos A/S
######

Principal Display Panel – 300 mg Carton Label

NDC 73594-0101-1

Rx only

Cosela®
(trilaciclib)
for injection

300 mg/vial*

For Intravenous Infusion
After Reconstitution
and Dilution

One Single-Dose Vial

Discard Unused Portion

Principal Display Panel – 300 mg Vial Label

NDC 73594-0101-1

Rx only

Cosela®
(trilaciclib)
for injection

300 mg/vial*

For Intravenous Infusion After
Reconstitution and Dilution

Single-Dose Vial